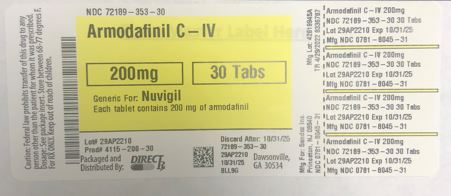 DRUG LABEL: ARMODAFINIL
NDC: 72189-353 | Form: TABLET
Manufacturer: DirectRx
Category: prescription | Type: HUMAN PRESCRIPTION DRUG LABEL
Date: 20250122
DEA Schedule: CIV

ACTIVE INGREDIENTS: ARMODAFINIL 200 mg/1 1
INACTIVE INGREDIENTS: POVIDONE K30; CROSCARMELLOSE SODIUM; STARCH, CORN; MAGNESIUM STEARATE; LACTOSE MONOHYDRATE; MICROCRYSTALLINE CELLULOSE

ARMODAFINIL

INDICATIONS AND USAGE

Armodafinil tablets are indicated to improve wakefulness in adult patients with excessive sleepiness associated with obstructive sleep apnea (OSA), narcolepsy, or shift work disorder (SWD).

Limitations of Use

In OSA, armodafinil tablets are indicated to treat excessive sleepiness and not as treatment for the underlying obstruction. If continuous positive airway pressure (CPAP) is the treatment of choice for a patient, a maximal effort to treat with CPAP for an adequate period of time should be made prior to initiating armodafinil tablets for excessive sleepiness.

DOSAGE FORMS AND STRENGTHS

2.1 Dosage in Obstructive Sleep Apnea (OSA) and Narcolepsy
The recommended dosage of armodafinil tablets for patients with OSA or narcolepsy is 150 mg to 250 mg taken orally once a day as a single dose in the morning.

In patients with OSA, doses up to 250 mg/day, given as a single dose, have been well tolerated, but there is no consistent evidence that these doses confer additional benefit beyond that of the 150 mg/day dose [see Clinical Pharmacology (12.3) and Clinical Studies (14.1, 14.2)].

2.2 Dosage in Shift Work Disorder (SWD)
The recommended dosage of armodafinil tablets for patients with SWD is 150 mg taken orally once a day as a single dose approximately 1 hour prior to the start of their work shift.

2.3 Dosage Modification in Patients with Severe Hepatic Impairment
In patients with severe hepatic impairment, the dosage of armodafinil tablets should be reduced [see Use in Specific Populations (8.6) and Clinical Pharmacology (12.3)].

2.4 Use in Geriatric Patients
Consideration should be given to the use of lower doses and close monitoring in geriatric patients [see Use in Specific Populations (8.5)].

DOSAGE FORMS AND STRENGTHS

50 mg – round, white to off-white tablet with
formw
on one side and "205" on the other
150 mg – oval, white to off-white tablet with
formw
on one side and "215" on the other
200 mg – rounded, rectangular, white to off-white tablet with
formw
on one side and "220" on the other
250 mg – oval, white to off-white tablet with
formw
on one side and "225" on the other

CONTRAINDICATIONS

Armodafinil is contraindicated in patients with known hypersensitivity to modafinil or armodafinil or its inactive ingredients [see Warnings and Precautions (5.1, 5.2, 5.3)].

WARNINGS AND PRECAUTIONS

5.1 Serious Dermatologic Reactions, including Stevens-Johnson Syndrome and Toxic Epidermal Necrosis
Serious rash requiring hospitalization and discontinuation of treatment has been reported in association with the use of armodafinil or modafinil (the racemic mixture of S- and R-enantiomers).

Armodafinil has not been studied in pediatric patients in any setting and is not approved for use in pediatric patients for any indication.

In clinical trials of modafinil, the incidence of rash resulting in discontinuation was approximately 0.8% (13 per 1,585) in pediatric patients (age <17 years); these rashes included 1 case of possible Stevens-Johnson syndrome (SJS) and 1 case of apparent multi-organ hypersensitivity reaction/Drug Rash with Eosinophilia and Systemic Symptoms (DRESS) [see Warnings and Precautions (5.2)]. Several of the cases were associated with fever and other abnormalities (e.g., vomiting, leukopenia). The median time to rash that resulted in discontinuation was 13 days. No such cases were observed among 380 pediatric patients who received placebo.

Skin and mouth sores, blistering, and ulceration have been reported with modafinil and armodafinil in the postmarketing setting. Recurrence of signs and symptoms of serious dermatologic reactions following rechallenge has been reported in some cases.

Rare cases of serious or life-threatening rash, including SJS and toxic epidermal necrolysis (TEN), have been reported in adults and children in worldwide postmarketing experience with modafinil and armodafinil.

There are no factors, including duration of therapy, that are known to predict the risk of occurrence or the severity of rash associated with modafinil or armodafinil. In cases where the time to onset was reported, serious rash occurred 1 day to 2 months after initiation of treatment, but isolated cases of serious dermatologic reactions have been reported with symptoms beginning after prolonged treatment (e.g., 3 months).

Although benign rashes also occur with armodafinil, it is not possible to reliably predict which rashes will prove to be serious. Accordingly, armodafinil should be discontinued at the first sign of rash, skin or mouth sores, or blistering or ulceration, unless the rash is clearly not drug-related. Discontinuation of treatment may not prevent a rash from becoming life-threatening or permanently disabling or disfiguring.

5.2 Drug Reaction with Eosinophilia and System Symptoms (DRESS)/Multiorgan Hypersensitivity
DRESS, also known as multi-organ hypersensitivity, has been reported with armodafinil. DRESS typically, although not exclusively, presents with fever, rash, lymphadenopathy, and/or facial swelling, in association with other organ system involvement, such as hepatitis, nephritis, hematologic abnormalities, myocarditis, or myositis, sometimes resembling an acute viral infection. Eosinophilia is often present. This disorder is variable in its expression, and other organ systems not noted here may be involved. It is important to note that early manifestations of hypersensitivity (e.g., fever, lymphadenopathy) may be present even though rash is not evident.

One fatal case of DRESS that occurred in close temporal association (3 weeks) with the initiation of armodafinil treatment has been reported in the postmarketing setting. In addition, multi-organ hypersensitivity reactions, including at least one fatality in postmarketing experience, have occurred in close temporal association (median time to detection 13 days; range 4-33) to the initiation of modafinil. Although there have been a limited number of reports, multi-organ hypersensitivity reactions may result in hospitalization or be life-threatening.

If a multi-organ hypersensitivity reaction is suspected, armodafinil should be discontinued. Although there are no case reports to indicate cross‑sensitivity with other drugs that produce this syndrome, the experience with drugs associated with multi-organ hypersensitivity would indicate this to be a possibility.

5.3 Angioedema and Anaphylaxis Reactions
Angioedema and hypersensitivity (with rash, dysphagia, and bronchospasm), were observed with armodafinil. Patients should be advised to discontinue therapy and immediately report to their physician any signs or symptoms suggesting angioedema or anaphylaxis (e.g., swelling of face, eyes, lips, tongue or larynx; difficulty in swallowing or breathing; hoarseness).

5.4 Persistent Sleepiness
Patients with abnormal levels of sleepiness who take armodafinil should be advised that their level of wakefulness may not return to normal. Patients with excessive sleepiness, including those taking armodafinil, should be frequently reassessed for their degree of sleepiness and, if appropriate, advised to avoid driving or any other potentially dangerous activity. Prescribers should also be aware that patients may not acknowledge sleepiness or drowsiness until directly questioned about drowsiness or sleepiness during specific activities.

5.5 Psychiatric Symptoms
In pre-approval narcolepsy, OSA and SWD controlled trials of armodafinil, anxiety, agitation, nervousness, and irritability were reasons for treatment discontinuation more often in patients on armodafinil compared to placebo (armodafinil 1.2% and placebo 0.3%). Depression was also a reason for treatment discontinuation more often in patients on armodafinil compared to placebo (armodafinil 0.6% and placebo 0.2%). Cases of suicidal ideation were observed in clinical trials.

Caution should be exercised when armodafinil is given to patients with a history of psychosis, depression, or mania. If psychiatric symptoms develop in association with armodafinil administration, consider discontinuing armodafinil.

Psychiatric adverse reactions have been reported in patients treated with modafinil. Modafinil and armodafinil are very closely related. Therefore, the incidence and type of psychiatric symptoms associated with armodafinil are expected to be similar to the incidence and type of these events with modafinil.

Postmarketing adverse reactions associated with the use of armodafinil, some of which have resulted in hospitalization, have included mania, delusions, hallucinations, suicidal ideation, and aggression. Many, but not all, patients who developed psychiatric adverse reactions had a prior psychiatric history. In these cases, reported armodafinil total daily doses ranged from 50 mg to 450 mg, which includes doses below and above the recommended dosages.

5.6 Effects on Ability to Drive and Use Machinery
Although armodafinil has not been shown to produce functional impairment, any drug affecting the central nervous system (CNS) may alter judgment, thinking or motor skills. Patients should be cautioned about operating an automobile or other hazardous machinery until it is reasonably certain that armodafinil therapy will not adversely affect their ability to engage in such activities.

5.7 Cardiovascular Events
In clinical studies of modafinil, cardiovascular adverse reactions, including chest pain, palpitations, dyspnea and transient ischemic T-wave changes on ECG were observed in three subjects in association with mitral valve prolapse or left ventricular hypertrophy. It is recommended that armodafinil tablets not be used in patients with a history of left ventricular hypertrophy or in patients with mitral valve prolapse who have experienced the mitral valve prolapse syndrome when previously receiving CNS stimulants. Findings suggestive of mitral valve prolapse syndrome include but are not limited to ischemic ECG changes, chest pain, or arrhythmia. If new onset of any of these findings occurs, consider cardiac evaluation.

Blood pressure monitoring in short term (≤3 months) pre-approval controlled trials of OSA, SWD, and narcolepsy showed small average increases in mean systolic and diastolic blood pressure in patients receiving armodafinil as compared to placebo (1.2 to 4.3 mmHg in the various experimental groups). There was also a slightly greater proportion of patients on armodafinil requiring new or increased use of antihypertensive medications (2.9%) compared to patients on placebo (1.8%). There was a small, but consistent, average increase in pulse rate over placebo in pre-approval controlled trials. This increase varied from 0.9 to 3.5 BPM. Increased monitoring of heart rate and blood pressure may be appropriate in patients on armodafinil. Caution should be exercised when prescribing armodafinil to patients with known cardiovascular disease.

ADVERSE REACTIONS

The following serious adverse reactions are described below and elsewhere in the labeling:
Serious Dermatologic Reactions [see Warnings and Precautions (5.1)]
Drug Reaction with Eosinophilia and System Symptoms (DRESS)/Multiorgan Hypersensitivity [see Warnings and Precautions (5.2)]
Angioedema and Anaphylaxis Reactions [see Warnings and Precautions (5.3)]
Persistent Sleepiness [see Warnings and Precautions (5.4)]
Psychiatric Symptoms [see Warnings and Precautions (5.5)]
Effects on Ability to Drive and Use Machinery [see Warnings and Precautions (5.6)]
Cardiovascular Events [see Warnings and Precautions (5.7)]
6.1 Clinical Trials Experience
Because clinical trials are conducted under widely varying conditions, adverse reaction rates observed in the clinical trials of a drug cannot be directly compared to rates in the clinical trials of another drug and may not reflect the rates observed in practice.
Armodafinil has been evaluated for safety in over 1,100 patients with excessive sleepiness associated with OSA, SWD, and narcolepsy.
Most Common Adverse Reactions
In the placebo-controlled clinical trials, the most common adverse reactions (≥5%) associated with the use of armodafinil more frequently than in placebo-treated patients were headache, nausea, dizziness, and insomnia. The adverse reaction profile was similar across the studies.
Table 1 presents the adverse reactions that occurred at a rate of 1% or more and were more frequent in armodafinil-treated patients than in placebo-treated patients in the placebo-controlled clinical trials.
Table 1 Adverse Reactions in Pooled Placebo-Controlled Clinical Trials* in OSA, Narcolepsy, and SWD with Armodafinil (150 mg and 250 mg)
Armodafinil
(%)
N=645 Placebo
(%)
N=445
*Adverse reactions that occurred in > 1% of armodafinil-treated patients and greater incidence than that of placebo.
Headache
17
9
Nausea
7
3
Dizziness
5
2
Insomnia
5
1
Anxiety
4
1
Diarrhea
4
2
Dry Mouth
4
1
Depression
2
0
Dyspepsia
2
0
Fatigue
2
1
Palpitations
2
1
Rash
2
0
Upper Abdominal Pain
2
1
Agitation
1
0
Anorexia
1
0
Constipation
1
0
Contact Dermatitis
1
0
Decreased Appetite
1
0
Depressed Mood
1
0
Disturbance In Attention
1
0
Dyspnea
1
0
Hyperhydrosis
1
0
Increased Gamma-Glutamyltransferase
1
0
Increased Heart Rate
1
0
Influenza-Like Illness
1
0
Loose Stools
1
0
Migraine
1
0
Nervousness
1
0
Pain
1
0
Paresthesia
1
0
Polyuria
1
0
Pyrexia
1
0
Seasonal Allergy
1
0
Thirst
1
0
Tremor
1
0
Vomiting
1
0
Dose-Dependent Adverse Reactions
In the placebo-controlled clinical trials which compared doses of 150 mg/day and 250 mg/day of armodafinil and placebo, the following adverse reactions were dose-related: headache, rash, depression, dry mouth, insomnia, and nausea. See Table 2 for additional information.
Table 2 Dose-Dependent Adverse Reactions in Pooled Placebo-Controlled Clinical Trials in OSA, Narcolepsy and SWD
Armodafinil
250 mg
(%)
N=198 Armodafinil
150 mg
(%)
N=447 Armodafinil
Combined
(%)
N=645
Placebo
(%)
N=445
Headache
23
14
17
9
Nausea
9
6
7
3
Insomnia
6
4
5
1
Dry Mouth
7
2
4
<1
Rash
4
1
2
<1
Depression
3
1
2
<1
Adverse Reactions Resulting in Discontinuation of Treatment
In placebo-controlled clinical trials, 44 of the 645 patients (7%) who received armodafinil discontinued due to an adverse reaction compared to 16 of the 445 (4%) of patients that received placebo. The most frequent reason for discontinuation was headache (1%).
Laboratory Abnormalities
Clinical chemistry, hematology, and urinalysis parameters were monitored in the studies. Mean plasma levels of gamma glutamyltransferase (GGT) and alkaline phosphatase (AP) were found to be higher following administration of armodafinil, but not placebo. Few patients, however, had GGT or AP elevations outside of the normal range. No differences were apparent in alanine aminotransferase (ALT), aspartate aminotransferase (AST), total protein, albumin, or total bilirubin, although there were rare cases of isolated elevations of AST and/or ALT. A single case of mild pancytopenia was observed after 35 days of treatment and resolved with drug discontinuation. A small mean decrease from baseline in serum uric acid compared to placebo was seen in clinical trials. The clinical significance of this finding is unknown.
6.2 Postmarketing Experience
The following adverse reactions have been identified during post approval use of armodafinil. Because these reactions are reported voluntarily from a population of uncertain size, it is not always possible to reliably estimate their frequency or establish a causal relationship to drug exposure.
Cardiovascular
Stroke
Gastrointestinal Disorders
Mouth Sores (including mouth blistering and ulceration)

DESCRIPTION

Armodafinil tablets are a wakefulness‑promoting agent for oral administration. Armodafinil is the R-enantiomer of modafinil which is a 1:1 mixture of the R- and S-enantiomers. The chemical name for armodafinil is 2‑[(R)-(diphenylmethyl)sulfinyl]acetamide. The molecular formula is C15H15NO2S and the molecular weight is 273.35.
The chemical structure is:
chemical structure
Armodafinil is a white to off-white, crystalline powder that is slightly soluble in water, sparingly soluble in acetone, and soluble in methanol.
Armodafinil tablets contain 50, 150, 200 or 250 mg of armodafinil and the following inactive ingredients: croscarmellose sodium, lactose monohydrate, magnesium stearate, microcrystalline cellulose, povidone, and pregelatinized starch.

OVERDOSAGE

Fatal overdoses involving modafinil alone or involving armodafinil or modafinil in combination with other drugs have been reported in the postmarketing setting. Symptoms most often accompanying armodafinil or modafinil overdose, alone or in combination with other drugs, have included anxiety, dyspnea, insomnia; central nervous system symptoms such as restlessness, disorientation, confusion, excitation and hallucination; digestive changes such as nausea and diarrhea; and cardiovascular changes such as tachycardia, bradycardia, hypertension, and chest pain.
No specific antidote exists for the toxic effects of an armodafinil overdose. Such overdoses should be managed with primarily supportive care, including cardiovascular monitoring.

16.1 How Supplied
Armodafinil tablets are available as follows:

50 mg
Each round, white to off-white tablet is debossed with formw on one side and "205" on the other.
NDC 0781-8029-31 – Bottles of 30

150 mg
Each oval, white to off-white tablet is debossed with formw on one side and "215" on the other.
NDC 0781-8037-31 – Bottles of 30

200 mg
Each rounded, rectangular, white to off-white tablet is debossed with C on one side and "220" on the other.
NDC 0781-8045-31 – Bottles of 30

250 mg
Each oval, white to off-white tablet is debossed with formw on one side and "225" on the other.
NDC 0781-8053-31 – Bottles of 30

16.2 Storage
Store at 20o to 25o C (68o to 77o F).

MEDICATION GUIDE

Armodafinil tablets, for oral use, C-IV
(are-moe-DAFF-ih-nil)
What is the most important information I should know about armodafinil tablets?
Armodafinil tablets are a federal controlled substance (C-IV) because it can be abused or lead to dependence. Keep armodafinil tablets in a safe place to prevent misuse and abuse. Selling or giving away armodafinil tablets may harm others, and is against the law. Tell your doctor if you have ever abused or been dependent on alcohol, prescription medicines or street drugs.

Armodafinil tablets may cause serious side effects including a serious rash or a serious allergic reaction that may affect parts of your body such as your liver or blood cells. Any of these may need to be treated in a hospital and may be life-threatening.

Stop taking armodafinil tablets and call your doctor right away or get emergency help if you have any of these symptoms:

skin rash, hives, sores in your mouth, or your skin blisters and peels
swelling of your face, eyes, lips, tongue, or throat
trouble swallowing, breathing or hoarseness
fever, shortness of breath, swelling of the legs, yellowing of the skin or whites of the eyes, or dark urine.
If you have a severe rash with armodafinil tablets, stopping the medicine may not keep the rash from becoming life-threatening or causing you to be permanently disabled or disfigured.

Armodafinil tablets are not approved for use in children for any medical condition.

It is not known if armodafinil tablets are safe and effective in children under the age of 18.
What are armodafinil tablets?
Armodafinil tablets are a prescription medicine used to improve wakefulness in adults who are very sleepy due to one of the following diagnosed sleep disorders:

narcolepsy
obstructive sleep apnea (OSA). Armodafinil tablets are used with other medical treatments for this sleep disorder. Armodafinil tablets do not take the place of using your CPAP machine or other treatments that your doctor has prescribed for this condition. It is important that you continue to use these treatments as prescribed by your doctor.
shift work disorder (SWD)
Armodafinil tablets will not cure these sleep disorders. Armodafinil tablets may help the sleepiness caused by these conditions, but it may not stop all your sleepiness. Armodafinil tablets do not take the place of getting enough sleep. Follow your doctor’s advice about good sleep habits and using other treatments.
Do not take armodafinil tablets if you:
are allergic to any of its ingredients. See the end of this Medication Guide for a complete list of ingredients in armodafinil tablets.
have had a rash or allergic reaction to either armodafinil tablets (NUVIGIL®) or modafinil (PROVIGIL®). These medicines are very similar.
Before you take armodafinil tablets, tell your doctor about all of your medical conditions, including if you:
have a history of mental health problems, including psychosis
have heart problems or had a heart attack
have high blood pressure. Your blood pressure may need to be checked more often while taking armodafinil tablets.
have liver or kidney problems
have a history of drug or alcohol abuse or addiction
are pregnant or planning to become pregnant. It is not known if armodafinil tablets will harm your unborn baby.
Pregnancy Registry: There is a registry for women who become pregnant during treatment with armodafinil tablets. The purpose of this registry is to collect information about the safety of armodafinil tablets during pregnancy. Contact the registry as soon as you learn that you are pregnant, or ask your doctor to contact the registry for you. You or your doctor can get information and enroll you in the registry by calling 1-866-404-4106.

are breastfeeding. It is not known if armodafinil passes into your milk. Talk to your doctor about the best way to feed your baby if you take armodafinil tablets.
Tell your doctor about all the medicines you take, including prescription and over-the-counter medicines, vitamins, and herbal supplements. Armodafinil tablets and many other medicines can interact with each other, sometimes causing side effects. Armodafinil tablets may affect the way other medicines work, and other medicines may affect how armodafinil tablets works. Your dose of armodafinil tablets or certain other medicines may need to be changed.
Especially, tell your doctor if you use or take:

a hormonal birth control method, such as birth control pills, shots, implants, patches, vaginal rings, and intrauterine devices (IUDs). Hormonal birth control methods may not work while you take armodafinil tablets. Women who use one of these methods of birth control may have a higher chance for getting pregnant while taking armodafinil tablets, and for one month after stopping armodafinil tablets. You should use effective birth control while taking armodafinil tablets and for one month after your final dose. Talk to your doctor about birth control choices that are right for you while taking armodafinil tablets.
Know the medicines you take. Keep a list of them and show it to your doctor and pharmacist when you get a new medicine. Your doctor or pharmacist will tell you if it is safe to take armodafinil tablets and other medicines together. Do not start any new medicines with armodafinil tablets unless your doctor has told you it is okay.
How should I take armodafinil tablets?

Take armodafinil tablets exactly as prescribed by your doctor. Your doctor will prescribe the dose of armodafinil tablets that is right for you. Do not change your dose of armodafinil tablets without talking to your doctor.
Your doctor will tell you the right time of day to take armodafinil tablets.
People with narcolepsy or OSA usually take armodafinil tablets one time each day in the morning.
People with SWD usually take armodafinil tablets about 1 hour before their work shift.
Do not change the time of day you take armodafinil tablets unless you have talked to your doctor. If you take armodafinil tablets too close to your bedtime, you may find it harder to go to sleep.
You can take armodafinil tablets with or without food.
If you take more than your prescribed dose or if you take an overdose of armodafinil tablets, call your doctor or poison control center right away.
Symptoms of an overdose of armodafinil tablets may include:

● Trouble sleeping ● Restlessness

● Confusion ● Feeling disoriented

● Feeling excited ● Hearing, seeing, feeling, or sensing things that are not really there (hallucinations)

● Nausea and diarrhea ● A fast or slow heartbeat

● Chest pain ● Increased blood pressure

● Anxiety ● Shortness of breath

What should I avoid while taking armodafinil tablets?
Do not drive a car or do other dangerous activities until you know how armodafinil tablets affect you. People with sleep disorders should always be careful about doing things that could be dangerous. Do not change your daily habits until your doctor tells you it is okay.
You should avoid drinking alcohol. It is not known how drinking alcohol will affect you when taking armodafinil tablets.
What are the possible side effects of armodafinil tablets?

Armodafinil tablets may cause serious side effects. Stop taking armodafinil tablets and call your doctor right away or get emergency help if you get any of the following:

a serious rash or serious allergic reaction. (See “What is the most important information I should know about armodafinil tablets?”)
mental (psychiatric) symptoms, including:
depression º feeling anxious
hearing, seeing, feeling, or sensing things º an extreme increase in activity and talking (mania)
that are not really there (hallucinations) º aggressive behavior
thoughts of suicide
other mental problems
symptoms of a heart problem, including chest pain, abnormal heart beats, and trouble breathing.
The most common side effects of armodafinil tablets include:

headache • nausea
dizziness • trouble sleeping
These are not all the possible side effects of armodafinil tablets.

Call your doctor for medical advice about side effects. You may report side effects to FDA at 1-800-FDA-1088.

How should I store armodafinil tablets?
Store armodafinil tablets at room temperature between 68° to 77°F (20° to 25°C).
Keep armodafinil tablets and all medicines out of the reach of children.
General information about the safe and effective use of armodafinil tablets.
Medicines are sometimes prescribed for purposes other than those listed in a Medication Guide. Do not use armodafinil tablets for a condition for which it was not prescribed. Do not give armodafinil tablets to other people, even if they have the same symptoms that you have. It may harm them and is against the law.

You can ask your pharmacist or healthcare provider for information about armodafinil tablets that is written for health professionals.
What are the ingredients in armodafinil tablets?
Active Ingredient: armodafinil

Inactive Ingredients: lactose monohydrate, microcrystalline cellulose, pregelatinized starch, croscarmellose sodium, povidone, and magnesium stearate.
This Medication Guide has been approved by the U.S. Food and Drug Administration.
Rev. October 2018

The brands listed are the registered trademarks of their respective owners and are not trademarks of Sandoz Inc.

Distributed by Sandoz Inc.
Princeton, NJ 08540